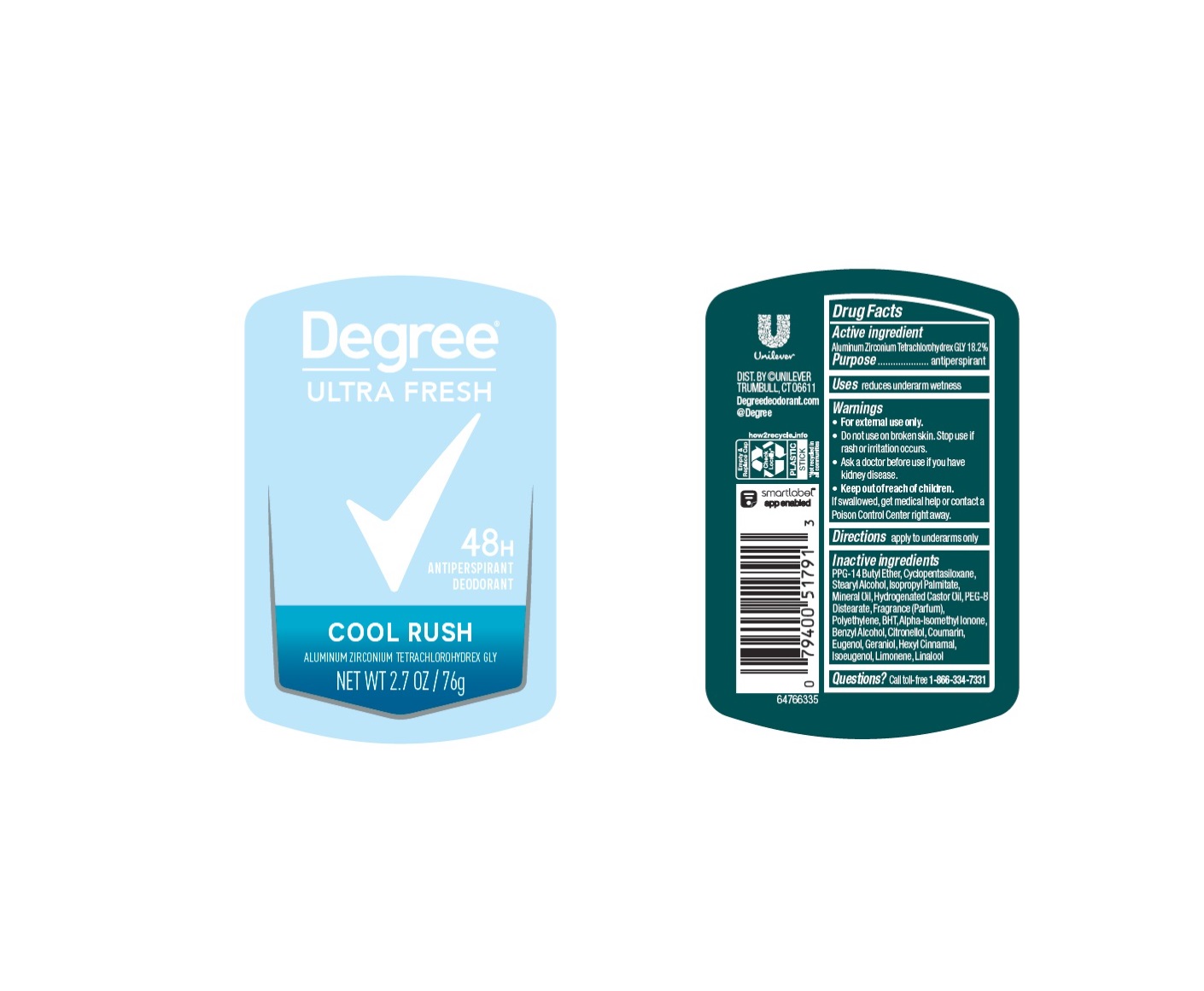 DRUG LABEL: Degree
NDC: 64942-2316 | Form: STICK
Manufacturer: Conopco Inc. d/b/a/ Unilever
Category: otc | Type: HUMAN OTC DRUG LABEL
Date: 20240613

ACTIVE INGREDIENTS: ALUMINUM ZIRCONIUM TETRACHLOROHYDREX GLY 18.2 g/100 g
INACTIVE INGREDIENTS: EUGENOL; LINALOOL, (+/-)-; ISOMETHYL-.ALPHA.-IONONE; CITRAL; MINERAL OIL; HYDROGENATED CASTOR OIL; CYCLOMETHICONE 5; BUTYLATED HYDROXYTOLUENE; PEG-8 DISTEARATE; ISOPROPYL PALMITATE; PPG-14 BUTYL ETHER; STEARYL ALCOHOL; .BETA.-CITRONELLOL, (R)-; BENZYL ALCOHOL; COUMARIN; GERANIOL; .ALPHA.-HEXYLCINNAMALDEHYDE; ISOEUGENOL; LIMONENE, (+)-; HIGH DENSITY POLYETHYLENE

Degree Cool Rush 48H Antiperspirant Deodorant

Drug Facts

Active ingredient

Aluminum Zirconium Tetrachlorohydrex GLY (18.2 %)

Purpose

antiperspirant

Uses

reduces underarm wetness

Warnings

• For external use only.
• Do not use on broken skin .
• Ask a doctor before use if you have kidney disease.
• Stop use if rash or irritation occurs.

• Keep out of reach of children.

If swallowed, get medical help or contact a Poison Control Center right away.

Directions

apply to underarms only

Inactive ingredients

PPG-14 Butyl Ether, Cyclopentasiloxane, Stearyl Alcohol, Isopropyl Palmitate, Mineral Oil, Hydrogenated Castor Oil, PEG-8 Distearate, Fragrance (Parfum), Polyethylene, BHT, Alpha-Isomethyl Ionone, Benzyl Alcohol, Citral, Citronellol, Coumarin, Eugenol, Geraniol, Hexyl Cinnamal, Isogenol, Limonene, Linalool

Questions?

Call toll-free 1-866-334-7331